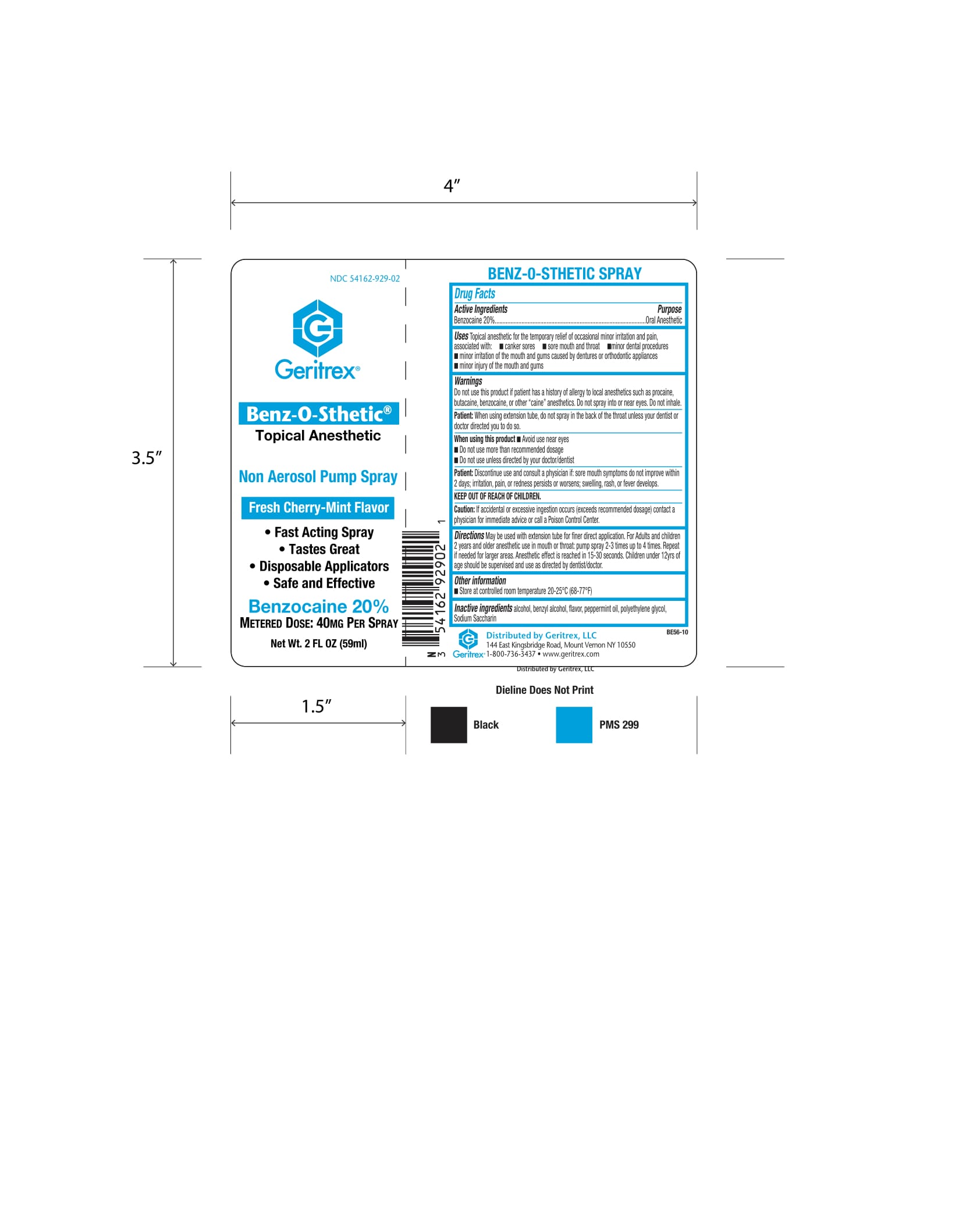 DRUG LABEL: Benz O Sthetic
NDC: 54162-929 | Form: SPRAY
Manufacturer: Geritrex LLC
Category: otc | Type: HUMAN OTC DRUG LABEL
Date: 20170928

ACTIVE INGREDIENTS: BENZOCAINE 11.8 g/59 mL
INACTIVE INGREDIENTS: BENZYL ALCOHOL; POLYETHYLENE GLYCOL 400; PEPPERMINT OIL; SACCHARIN SODIUM

Benz-O-Sthetic Spray

Drugs Facts

Active Ingredients Purpose
Benzocaine 20%........................Oral Anesthetic

Uses

Topical anesthetic for the temporary relief of occasional minor irritation and pain, associated with:
canker sores

- sore mouth and throat
- minor dental procedures
- minor irritation of the mouth and gums caused by dentures or orthodontic appliances
- minor injury of the mouth and gums

Directions

May be used with extension tube for finer direct application. For adults and children 2 years and older anesthetic use in mouth or throat:
Pump spray 2-3 times up to 4 times. Repeat if needed for larger areas. Anesthetic effect is reached in 15-30 seconds. Children under 12 years of age should be supervised and use as directed by dentist/doctor.

Warnings

Do not use this product if patient has a history of allergy to local anesthetics
such as procaine, butacaine, benzocaine, or other “caine” anesthetics. Do not
spray into or near eyes. Do not inhale.

Patient: When using extension tube, do not spray in the back of the throat
unless your dentist or doctor directed you to do so.

When using this product:

- Avoid use near eyes
- Do not use more than recommended dosage
- Do not go beyond 7 days usage, unless directed by your doctor/dentist

Patient: Discontinue use and consult a physician if: sore mouth symptoms do
not improve in 5 days; irritation, pain, or redness persists or worsens;
swelling, rash, or fever develops.

Other Ingredients

Alcohol, benzyl alcohol, flavor, peppermint oil, polyethylene glycol, sodium saccharin

Other Information:

store at controlled room temperature 20-25°C (68-77°F)

KEEP OUT OF REACH OF CHILDREN

WARNINGS AND PRECAUTIONS

Caution: If accidental or excessive ingestion occurs (exceeds recommended dosage) contact a physician for immediate advice or call a Poison Control Center.